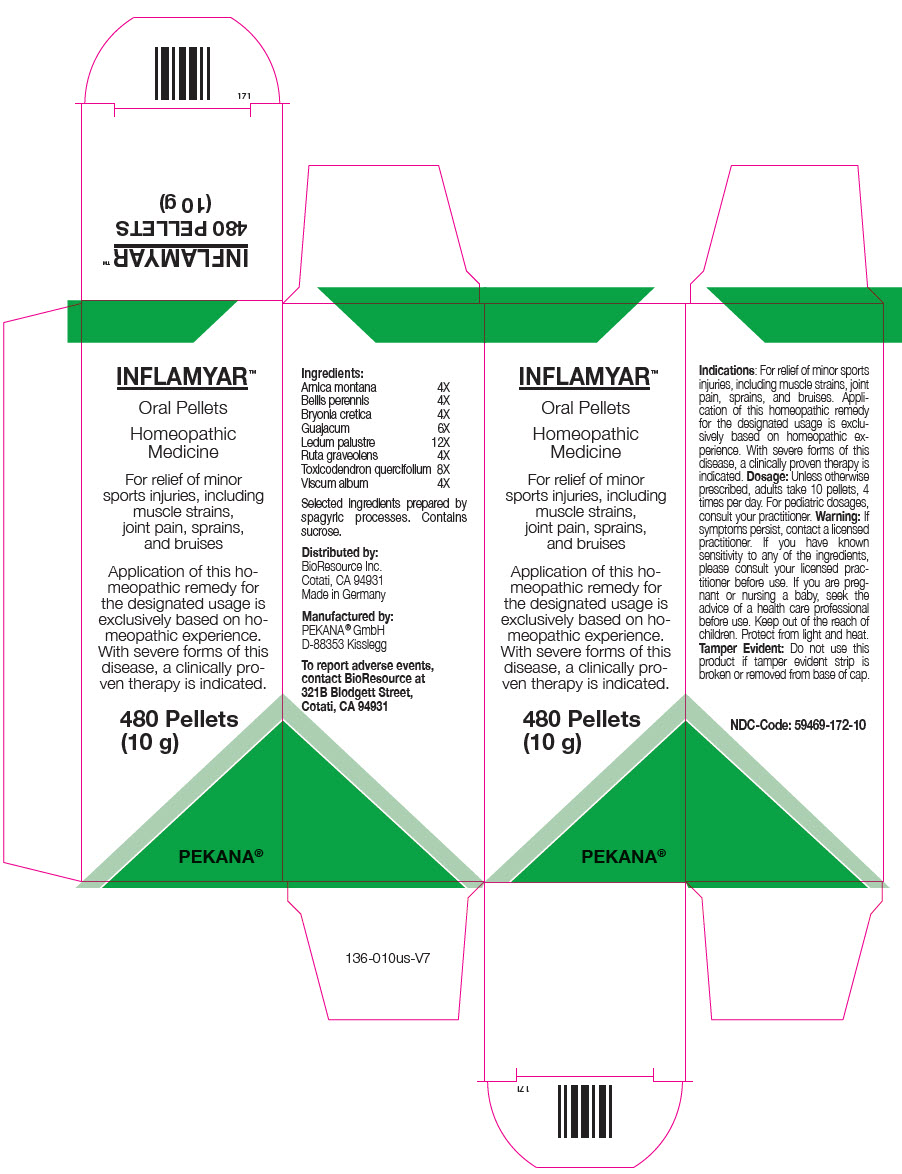 DRUG LABEL: Inflamyar
NDC: 59469-172 | Form: PELLET
Manufacturer: Pekana-Naturheilmittel GmbH
Category: homeopathic | Type: HUMAN OTC DRUG LABEL
Date: 20221215

ACTIVE INGREDIENTS: ARNICA MONTANA WHOLE 4 [hp_X]/1 1; BELLIS PERENNIS WHOLE 4 [hp_X]/1 1; BRYONIA DIOICA ROOT 4 [hp_X]/1 1; GUAIACUM OFFICINALE RESIN 6 [hp_X]/1 1; RHODODENDRON TOMENTOSUM LEAFY TWIG 12 [hp_X]/1 1; RUTA GRAVEOLENS WHOLE 4 [hp_X]/1 1; TOXICODENDRON PUBESCENS LEAF 8 [hp_X]/1 1; VISCUM ALBUM FRUIT 4 [hp_X]/1 1
INACTIVE INGREDIENTS: SUCROSE

INFLAMYAR™
Pellets

PURPOSE

for sports injuries and joint pain

Ingredients

Arnica montana | 4X
Bellis perennis | 4X
Bryonia cretica | 4X
Guajacum | 6X
Ledum palustre | 12X
Ruta graveolens | 4X
Toxicodendron quercifolium | 8X
Viscum album | 4X

INACTIVE INGREDIENT

Selected ingredients prepared by spagyric processes. Contains sucrose.

Indications

For relief of minor sports injuries, including muscle strains, joint pain, sprains, and bruises. Application of this homeopathic remedy for the designated usage is exclusively based on homeopathic experience. With severe forms of this disease, a clinically proven therapy is indicated.

Dosage

Unless otherwise prescribed, adults take 10 pellets, 4 times per day. For pediatric dosages, consult your practitioner.

Warning

If symptoms persist, contact a licensed practitioner. If you have known sensitivity to any of the ingredients, please consult your licensed practitioner before use. If you are pregnant or nursing a baby, seek the advice of a health care professional before use.

Keep out of the reach of children.

STORAGE AND HANDLING

Protect from light and heat.

Tamper Evident

Do not use this product if tamper evident strip is broken or removed from base of cap.

To report adverse events, contact BioResource at 321B Blodgett Street, Cotati, CA 94931

Manufactured by:
PEKANA® GmbH
D-88353 Kisslegg

Distributed by:
BioResource Inc.
Cotati, CA 94931
Made in Germany

PRINCIPAL DISPLAY PANEL - 10 g Bottle Carton

INFLAMYAR™

Oral Pellets

Homeopathic
Medicine

For relief of minor
sports injuries, including
muscle strains,
joint pain, sprains,
and bruises

Application of this ho-
meopathic remedy for
the designated usage is
exclusively based on ho-
meopathic experience.
With severe forms of this
disease, a clinically pro-
ven therapy is indicated.

480 Pellets
(10 g)

PEKANA®